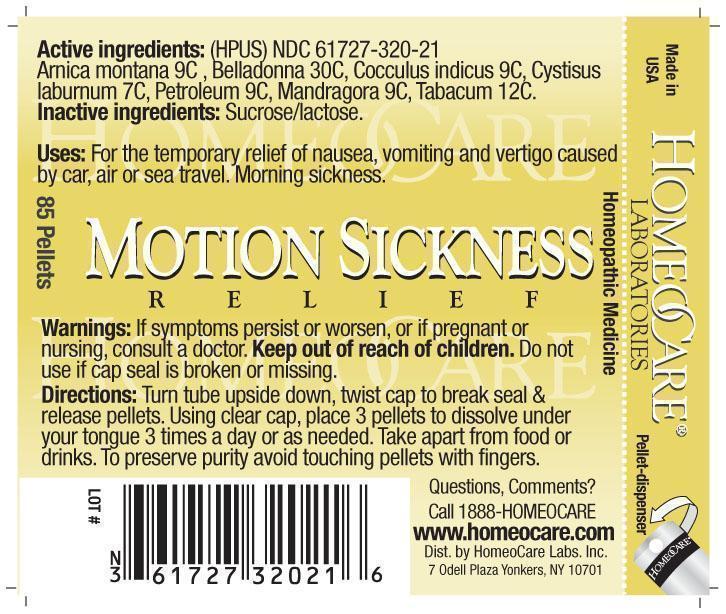 DRUG LABEL: Motion Sickness Relief
NDC: 61727-320 | Form: PELLET
Manufacturer: Homeocare Laboratories
Category: homeopathic | Type: HUMAN OTC DRUG LABEL
Date: 20210113

ACTIVE INGREDIENTS: ARNICA MONTANA 9 [hp_C]/4 g; ATROPA BELLADONNA 30 [hp_C]/4 g; ANAMIRTA COCCULUS SEED 9 [hp_C]/4 g; LABURNUM ANAGYROIDES FLOWERING TOP 7 [hp_C]/4 g; LIQUID PETROLEUM 9 [hp_C]/4 g; MANDRAGORA OFFICINARUM ROOT 9 [hp_C]/4 g; TOBACCO LEAF 12 [hp_C]/4 g
INACTIVE INGREDIENTS: SUCROSE; LACTOSE

Motion Sickness Relief

Active ingredients:

Arnica montana 9C, Belladonna 30C, Cocculus indicus 9C, Cystisus laburnum 7C, Petroleum 9C, Mandragora 9C, Tabacum 12C.

Purpose:

For the temporary relief of nausea, vomiting and vertigo caused by car, air or sea travel. Morning sickness.

Keep out of reach of children.

Indications & Usage:

Turn tube upside down, twist cap to break seal & release pellets. Using clear cap, place 3 pellets to dissolve under your tongue 3 times a day or as needed. Take apart from food or drinks. To preserve purity avoid touching pellets with fingers.

Warnings:

If symptoms persist or worsen, or if pregnant or nursing, consult a doctor. Keep out of reach of children. Do not use if cap seal is broken or missing.

Dosage & Administration:

Turn tube upside down, twist cap to break seal & release pellets. Using clear cap, place 3 pellets to dissolve under your tongue 3 times a day or as needed. Take apart from food or drinks. To preserve purity avoid touching pellets with fingers.

Inactive ingredients:

Sucrose/lactose.

Motion Sickness Relief

Homeopathic Medicine

85 Pellets

hcl_label_motion 2012.jpg